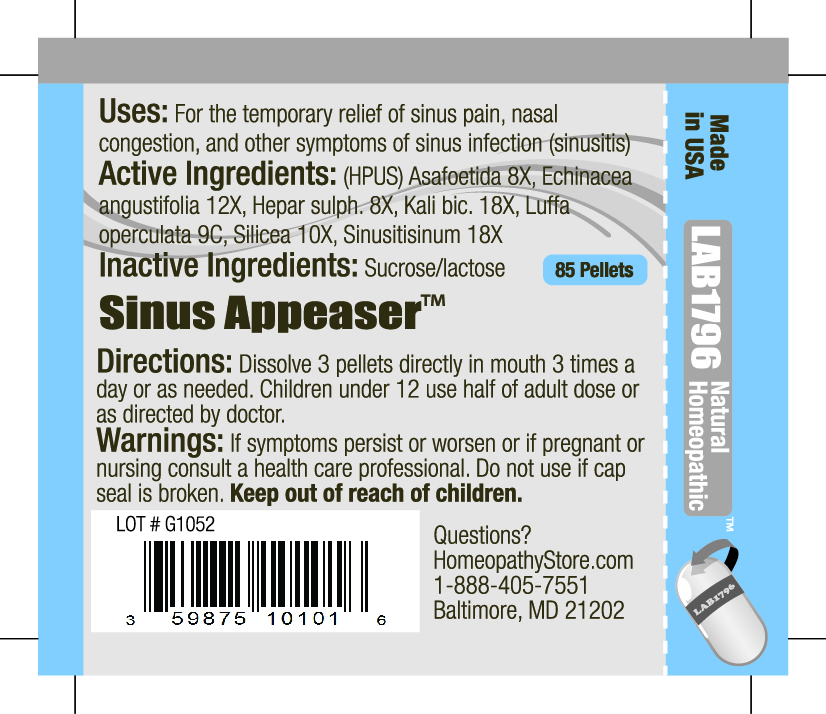 DRUG LABEL: Lab1796 Sinus Appeaser
NDC: 59875-1010 | Form: PELLET
Manufacturer: HomeopathyStore.com
Category: homeopathic | Type: HUMAN OTC DRUG LABEL
Date: 20101230

ACTIVE INGREDIENTS: ASAFETIDA 8 [hp_X]/1 1; ECHINACEA ANGUSTIFOLIA 12 [hp_X]/1 1; CALCIUM SULFIDE 8 [hp_X]/1 1; POTASSIUM DICHROMATE 18 [hp_X]/1 1; LUFFA OPERCULATA FRUIT 9 [hp_C]/1 1; SILICON DIOXIDE 10 [hp_X]/1 1; SINUSITISINUM 18 [hp_X]/1 1
INACTIVE INGREDIENTS: SUCROSE; LACTOSE

Sinus Appeaser

Uses:

For the temporary relief of sinus pain, nasal congestion, and other symptoms of sinus infection (sinusitis)

Active Ingredients:

(HPUS) Asafoetida 8X, Echinacea angustifolia 12X, Hepar sulph. 8X, Kali bic. 18X, Luffa operculata 9C, Silicea 10X, Sinusitisinum 18X

Inactive Ingredients:

Sucrose/lactose

Directions:

DOSAGE AND ADMINISTRATION

Dissolve 3 pellets directly in mouth 3 times a day or as needed. Children under 12 use half of adult dose or as directed by doctor.

Warnings:

If symptoms persist or worsen or if pregnant or nursing consult a health care professional. Do not use if cap seal is broken.

Keep out of reach of children.